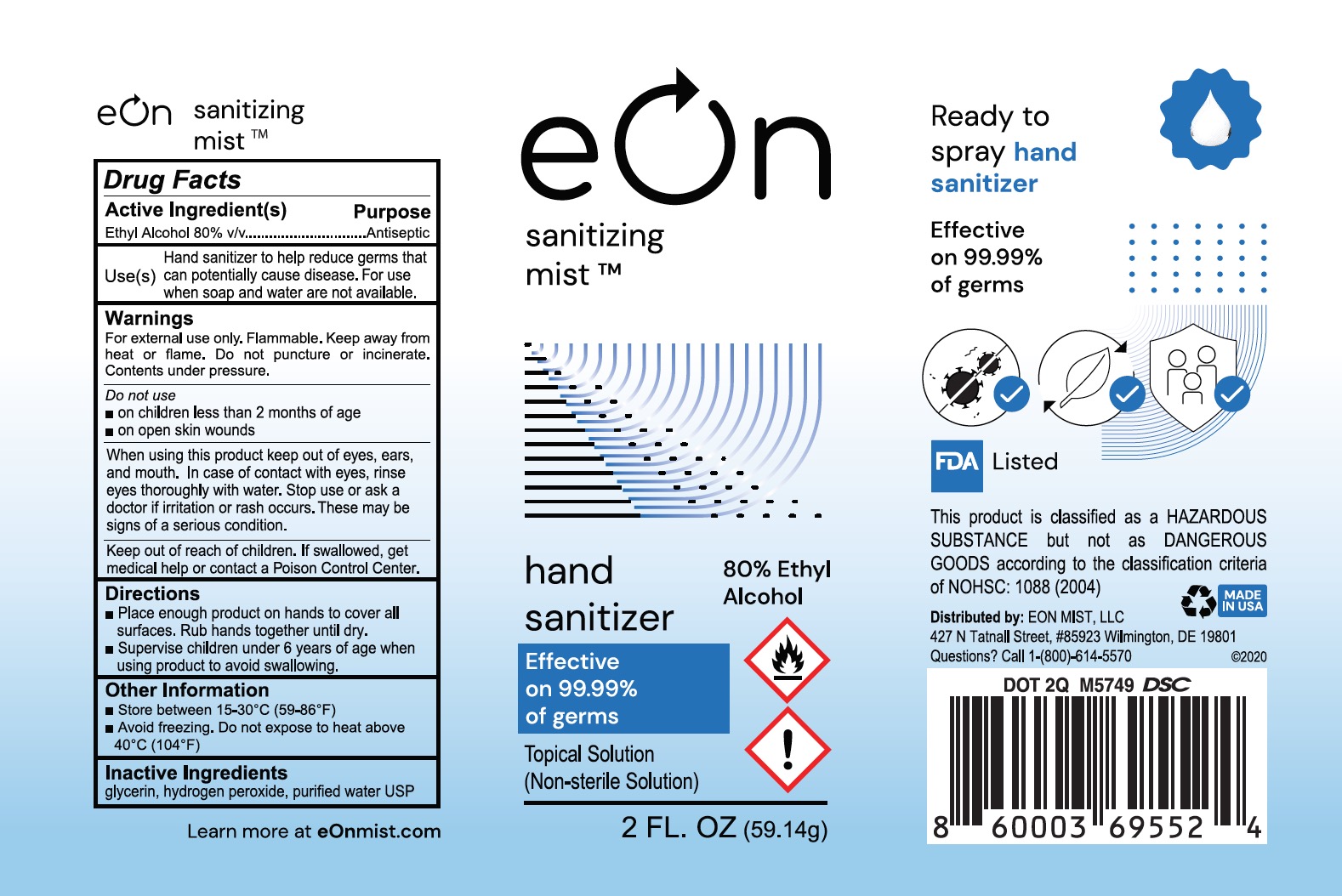 DRUG LABEL: EON Hand Sanitizing Mist TM
NDC: 73787-135 | Form: SPRAY
Manufacturer: FGD, LLC
Category: otc | Type: HUMAN OTC DRUG LABEL
Date: 20210106

ACTIVE INGREDIENTS: ALCOHOL 80 mL/100 mL
INACTIVE INGREDIENTS: WATER; GLYCERIN; HYDROGEN PEROXIDE

EON Hand Sanitizing Mist TM (59.14 mL)

ACTIVE INGREDIENT

Ethyl Alcohol 80% v/v

PURPOSE

Antiseptic

INDICATIONS AND USAGE

Hand sanitizer to help reduce germs that can potentially cause disease. For use when soap and water are not available

WARNINGS

For external use only. Flammable. Keep away from heat or flame. Do not puncture or incinerate. Contents under pressure.

DO NOT USE

- on children less than 2 months of age
- on open skin wounds

WHEN USING

keep out of eyes, ears, and mouth. In case of contact with eyes, rinse eyes thoroughly with water.

STOP USE

if irritation or rash occurs. These may be signs of a serious condition.

KEEP OUT OF REACH OF CHILDREN

If swallowed, get medical help or contact a Poison Control Center.

DOSAGE AND ADMINISTRATION

- Place enough product on hands to cover all surfaces. Rub hands together until dry.
- Supervise children under 6 years of age when using hit produce to avoid swallowing.

OTHER SAFETY INFORMATION

- Store between 15-30oC (59-86oF)
- Avoid freezing. Do not expose to heat above 40oC (104oF)

INACTIVE INGREDIENT

Glycerin, Hydrogen Peroxide, Purified Water